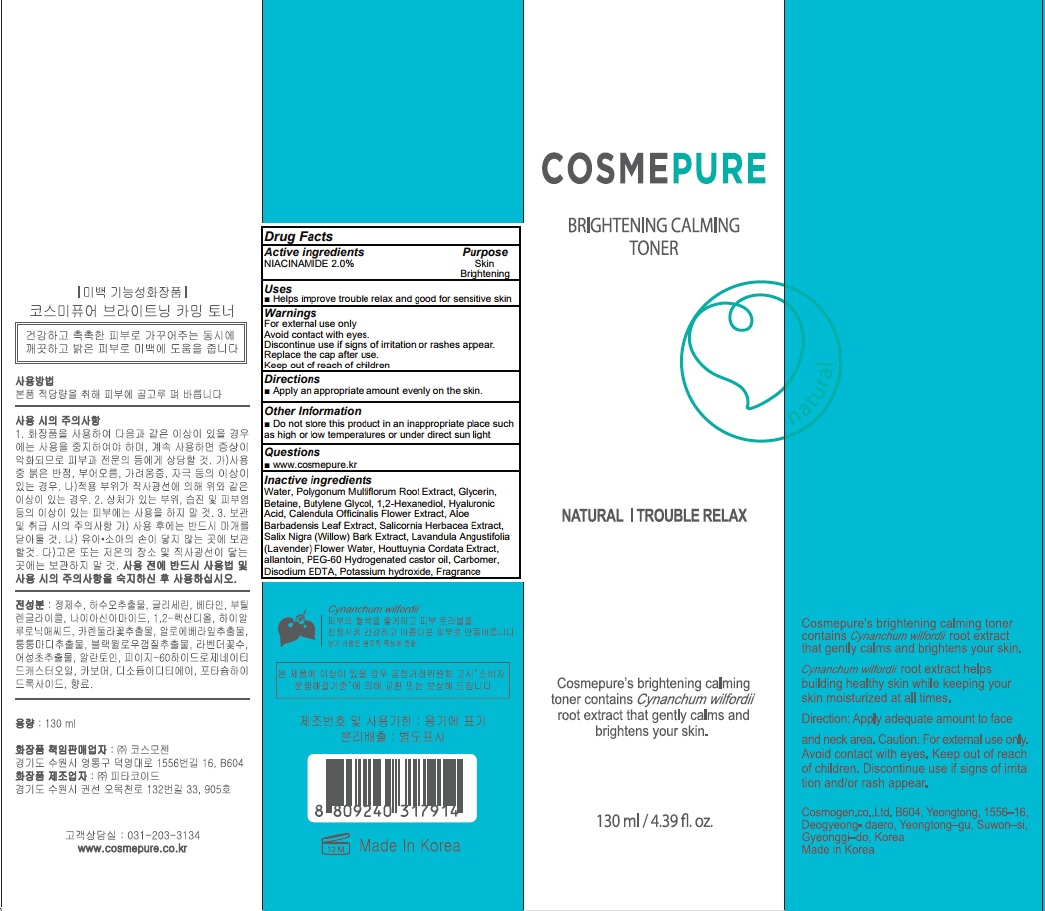 DRUG LABEL: COSMEPURE BRIGHTENING CALMING TONER
NDC: 81418-080 | Form: LIQUID
Manufacturer: Cosmogen Co., Ltd.
Category: otc | Type: HUMAN OTC DRUG LABEL
Date: 20210304

ACTIVE INGREDIENTS: Niacinamide 2.6 g/130 mL
INACTIVE INGREDIENTS: Water; REYNOUTRIA MULTIFLORA ROOT; Glycerin

ACTIVE INGREDIENT

Niacinamide 2.0%

INACTIVE INGREDIENTS

Water, Polygonum Multiflorum Root Extract, Glycerin, Betaine, Butylene Glycol, 1,2-Hexanediol, Hyaluronic Acid, Calendula Officinalis Flower Extract, Aloe Barbadensis Leaf Extract, Salicornia Herbacea Extract, Salix Nigra (Willow) Bark Extract, Lavandula Angustifolia (Lavender) Flower Water, Houttuynia Cordata Extract, allantoin, PEG-60 Hydrogenated castor oil, Carbomer, Disodium EDTA, Potassium hydroxide, Fragrance

PURPOSE

Skin brightening

WARNINGS

For external use only
Avoid contact with eyes.
Discontinue use if signs of irritation or rashes appear.
Replace the cap after use.
Keep out of reach of children

KEEP OUT OF REACH OF CHILDREN

Uses

■ Helps improve trouble relax and good for sensitive skin

Directions

■ Apply an appropriate amount evenly on the skin.

Other information

■ Do not store this product in an inappropriate place such as high or low temperatures or under direct sun light

QUESTIONS

■ www.cosmepure.kr